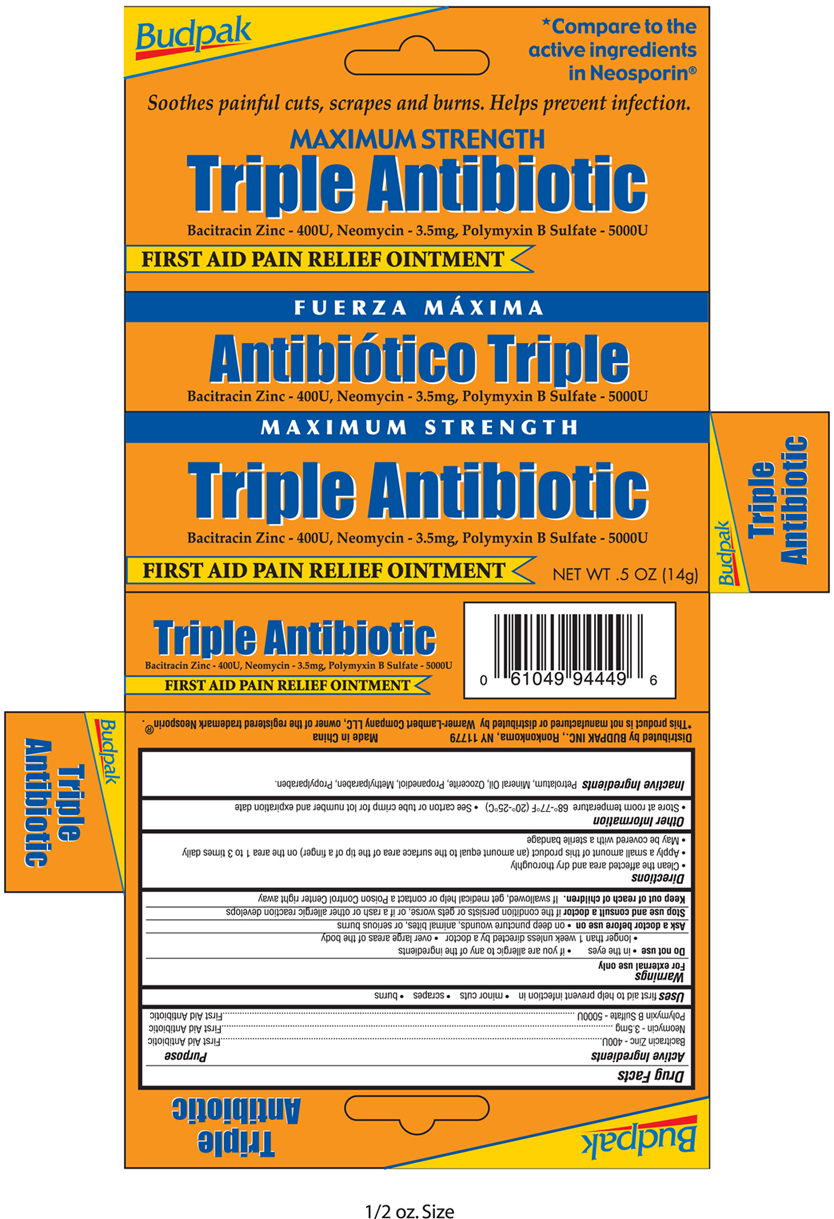 DRUG LABEL: Triple Antibiotic
NDC: 27293-014 | Form: OINTMENT
Manufacturer: Budpak Inc. 
Category: otc | Type: HUMAN OTC DRUG LABEL
Date: 20110816

ACTIVE INGREDIENTS: BACITRACIN ZINC 400 [USP'U]/1 g; NEOMYCIN  3.5 mg/1 g; POLYMYXIN B SULFATE 5000 [USP'U]/1 g
INACTIVE INGREDIENTS: PETROLATUM; MINERAL OIL; PROPANEDIOL; METHYLPARABEN; PROPYLPARABEN

Drug Facts

Active Ingredients
Bacitracin Zinc 400U
Neomycin 3.5mg
Polymyxin B sulfate 5000U

Purpose
First Aid Antibiotic
First Aid Antibiotic
First Aid Antibiotic

INDICATIONS AND USAGE

Uses first aid to help prevent infection in •minor cuts •scrapes •burns

Warnings
For external use only

Do not use •in the eyes •if you are allergic to any of the ingredients •longer than 1 week unless directed by a doctor •over large areas of the body

Ask a doctor before use on •on deep puncture wounds, animal bites, or serious burns

Stop use and consult a doctor if the condition persists or gets worse, or if a rash or other allergic reaction develops

Keep out of reach of children. If swallowed, get medical help or contact a Poison Control Center right away.

Directions
•Clean the affected area and dry thoroughly
•Apply a small amount of this product (an amount equal to the surface area of the tip of a finger) on the area 1 to 3 times daily
•May be covered with a sterile bandage

Other information
•Store at 68 to 77F (20C-25C) •See carton or tube crimp for lot number and expiration date

INACTIVE INGREDIENT

Inactive ingredients Petrolatum, Mineral oil, Ozocerite, Propanediol, Methylparaben, Propylparaben

Package Label